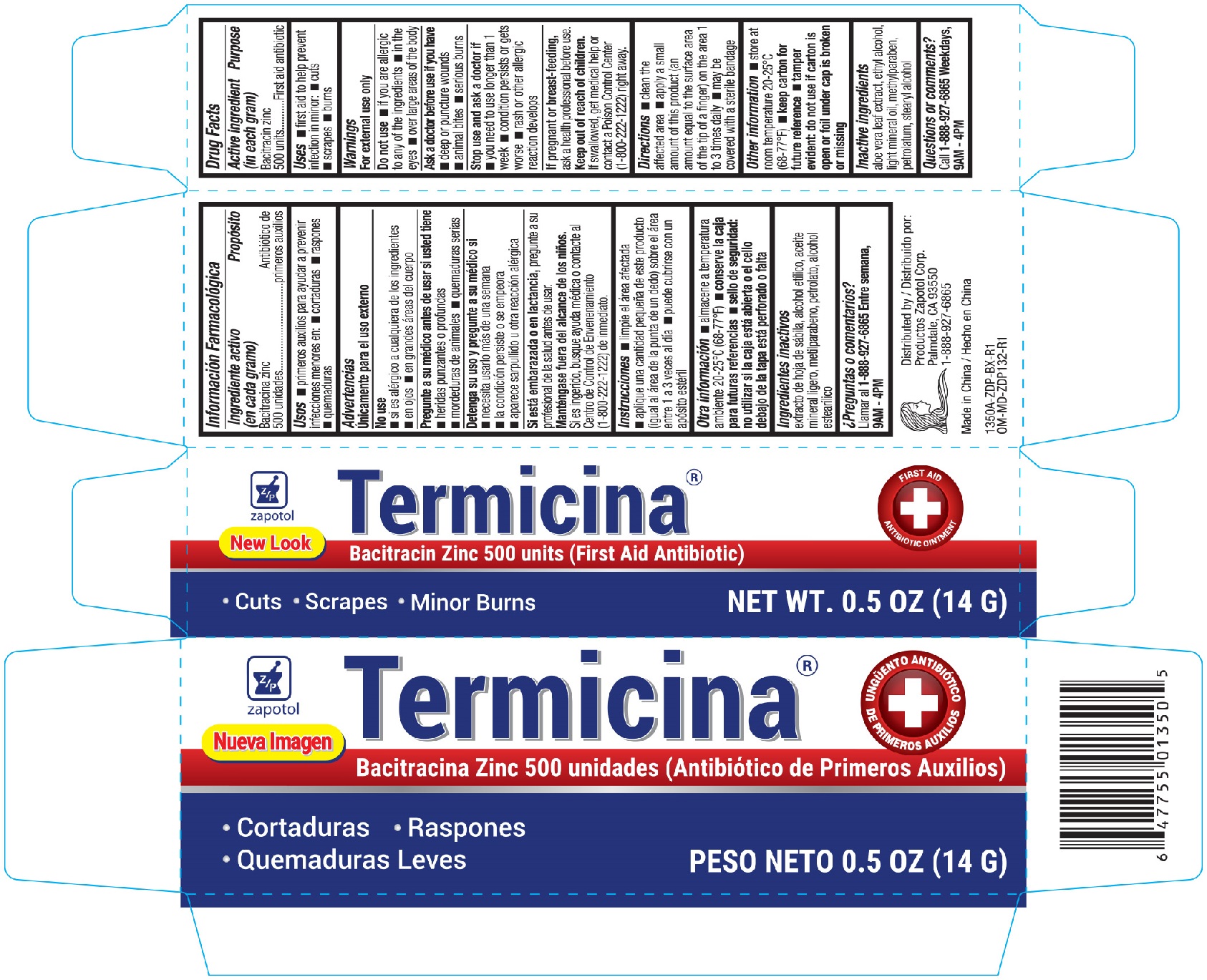 DRUG LABEL: Zapotol Bacitracin
NDC: 59428-135 | Form: CREAM
Manufacturer: Zapatol Corp.
Category: otc | Type: HUMAN OTC DRUG LABEL
Date: 20251022

ACTIVE INGREDIENTS: BACITRACIN 500 [USP'U]/1 g
INACTIVE INGREDIENTS: ALOE VERA LEAF; LIGHT MINERAL OIL; PETROLATUM; STEARYL ALCOHOL; METHYLPARABEN; ALCOHOL

Zapotol Termicina Antibiotic Ointment 0.5oz 1350A ZDP

Active ingredient (each gram contains) Purpose

Bacitracin 500 units.....................................................................First Aid Antibiotic

Uses

First aid to help prevent infection in

- minor cuts
- scrapes
- burns

Warnings

For external use only

Do not use

- in the eyes
- over large areas of the body
- if you are allergic to any of the ingredients

Ask a doctor before useif

- you need to use longer than 1 week
- condition persists or gets worse
- rash or other allergic reaction develops

Stop use and ask a doctor if

- the condition persists or gets worse
- a rash or other allergic reaction develops

PREGNANCY OR BREAST FEEDING

If pregnant or breast-feeding, ask a health professional before use.

Keep out of reach of children

If swallowed, get medical help or contact a Poison Control Center (1-800-222-1222) right away.

Directions

- clean the affected area
- apply a small amount of this product (an amount equal to the surface area of the tip of a finger) on the area 1 to 3 times daily
- may be covered with a sterile bandage

Other Information

- Store at 20°C to 25°C (68°F to 77°F)
- keep carton for future reference
- tamper evident: do not use if carton or foil under cap is broker or missing

Inactive ingredients

aloe vera leaf extract, ethyl alcohol, light mineral oil, methylparaben, petrolatum, stearyl alcohol

DOSAGE AND ADMINISTRATION

DISTRIBUTED BY:

Productos Zapotol Corp.

Palmdate, CA

Made in China